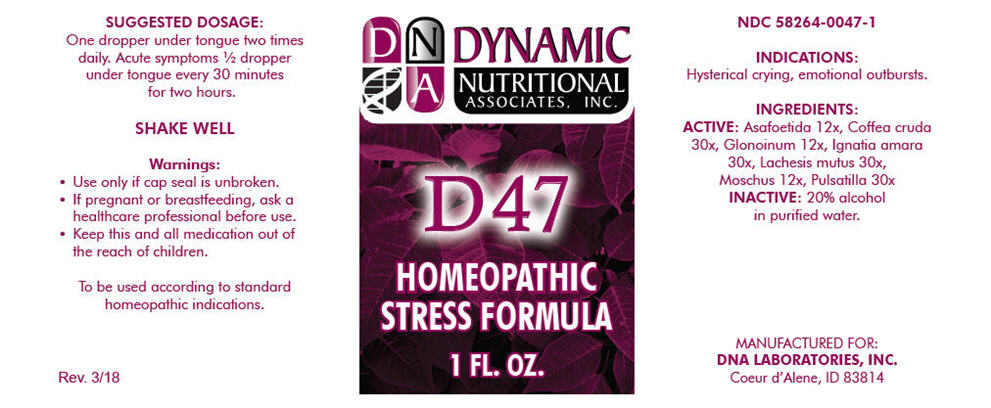 DRUG LABEL: D-47
NDC: 58264-0047 | Form: SOLUTION
Manufacturer: DNA Labs, Inc.
Category: homeopathic | Type: HUMAN OTC DRUG LABEL
Date: 20250113

ACTIVE INGREDIENTS: FERULA ASSA-FOETIDA RESIN 12 [hp_X]/1 mL; ARABICA COFFEE BEAN 30 [hp_X]/1 mL; NITROGLYCERIN 12 [hp_X]/1 mL; STRYCHNOS IGNATII SEED 30 [hp_X]/1 mL; LACHESIS MUTA VENOM 30 [hp_X]/1 mL; MOSCHUS MOSCHIFERUS MUSK SAC RESIN 12 [hp_X]/1 mL; ANEMONE PRATENSIS 30 [hp_X]/1 mL
INACTIVE INGREDIENTS: ALCOHOL; WATER

D-47

NDC 58264-0047-1

INDICATIONS

PURPOSE

Hysterical crying, emotional outbursts.

INGREDIENTS

ACTIVE

Asafoetida 12x, Coffea cruda 30x, Glonoinum 12x, Ignatia amara 30x, Lachesis mutus 30x, Moschus 12x, Pulsatilla 30x

INACTIVE

20% alcohol in purified water.

SUGGESTED DOSAGE

One dropper under tongue two times daily. Acute symptoms ½ dropper under tongue every 30 minutes for two hours.

SHAKE WELL

Warnings

- Use only if cap seal is unbroken.

PREGNANCY OR BREAST FEEDING

- If pregnant or breastfeeding, ask a healthcare professional before use.

KEEP OUT OF REACH OF CHILDREN

- Keep this and all medication out of the reach of children.

To be used according to standard homeopathic indications.

PRINCIPAL DISPLAY PANEL - 1 FL. OZ. Bottle Label

DYNAMIC
NUTRITIONAL
ASSOCIATES, INC.

D 47

HOMEOPATHIC
STRESS FORMULA

1 FL. OZ.